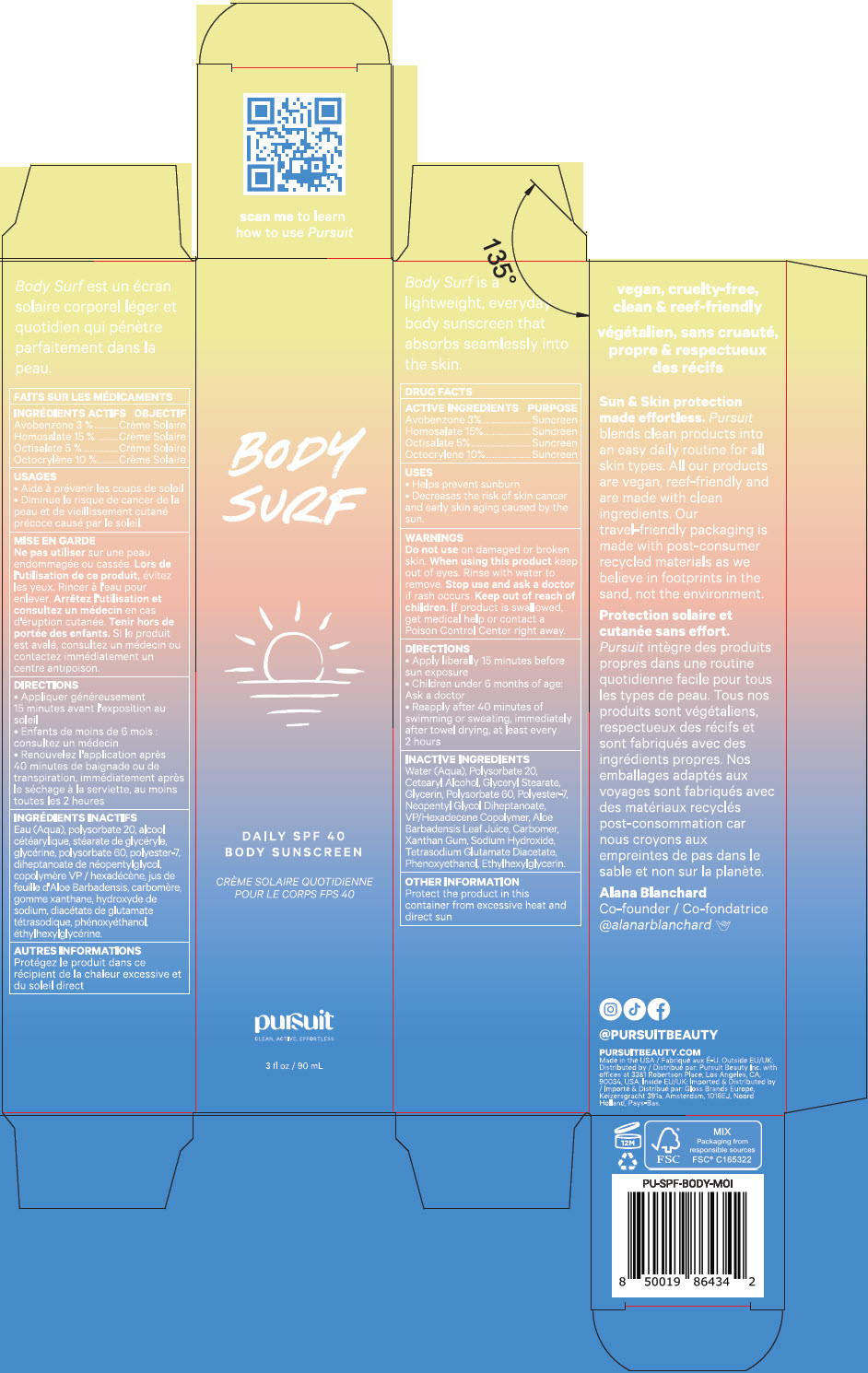 DRUG LABEL: Pursuit Body Surf Daily SPF 40 Body Sunscreen
NDC: 83040-001 | Form: LOTION
Manufacturer: Pursuit Beauty Inc.
Category: otc | Type: HUMAN OTC DRUG LABEL
Date: 20221202

ACTIVE INGREDIENTS: AVOBENZONE 3 g/100 g; HOMOSALATE 15 g/100 g; OCTISALATE 5 g/100 g; OCTOCRYLENE 10 g/100 g
INACTIVE INGREDIENTS: WATER 43.06 g/100 g; POLYSORBATE 20 5 g/100 g; CETOSTEARYL ALCOHOL 3.2 g/100 g; GLYCERYL MONOSTEARATE 3.2 g/100 g; GLYCERIN 3 g/100 g; POLYSORBATE 60 2.5 g/100 g; POLYESTER-7 2.2 g/100 g; NEOPENTYL GLYCOL DIHEPTANOATE 1.8 g/100 g; VINYLPYRROLIDONE/HEXADECENE COPOLYMER 1.2 g/100 g; ALOE VERA LEAF 0.28 g/100 g; CARBOMER HOMOPOLYMER, UNSPECIFIED TYPE 0.28 g/100 g; XANTHAN GUM 0.13 g/100 g; SODIUM HYDROXIDE 0.12 g/100 g; TETRASODIUM GLUTAMATE DIACETATE 0.03 g/100 g; PHENOXYETHANOL 0.86 g/100 g; ETHYLHEXYLGLYCERIN 0.14 g/100 g

Pursuit Body Surf Daily SPF 40 Body Sunscreen

Drug Facts

ACTIVE INGREDIENT

Active Ingredients | Purpose
Avobenzone (3.0%) | Sunscreen
Homosalate (15.0%) | Sunscreen
Octisalate (5.0%) | Sunscreen
Octocrylene (10.0%) | Sunscreen

Uses

- helps prevent sunburn
- decreases the risk of skin cancer and early skin aging caused by the sun.

Warnings

Do not use on damaged or broken skin

When using this product keep out of eyes. Rinse with water to remove

Stop use and ask a doctor if rash occurs

Keep out of reach of children. If product is swallowed, get medical help or contact a Poison Control Center right away.

Directions

- apply liberally 15 minutes before sun exposure
- children under 6 months of age: Ask a doctor
- reapply after 40 minutes of swimming or sweating, immediately after towel drying, at least every 2 hours

Inactive Ingredients

Water (Aqua), Polysorbate 20, Cetearyl Alcohol, Glyceryl Stearate, Glycerin, Polysorbate 60, Polyester-7, Neopentyl Glycol Diheptanoate, VP/Hexadecene Copolymer, Aloe Barbadensis Leaf Juice, Carbomer, Xanthan Gum, Sodium Hydroxide, Tetrasodium Glutamate Diacetate, Phenoxyethanol, Ethylhexylglycerin.

Other Information

Protect the product in this container from excessive heat and direct sun

Distributed by:
Pursuit Beauty Inc. with
offices at 3381 Robertson Place, Los Angeles, CA,
90034, USA.

PRINCIPAL DISPLAY PANEL - 90 mL Tube Carton

BODY SURF

DAILY SPF 40
BODY SUNSCREEN

pursuit
CLEAN, ACTIVE, EFFORTLESS

3 fl oz / 90 mL